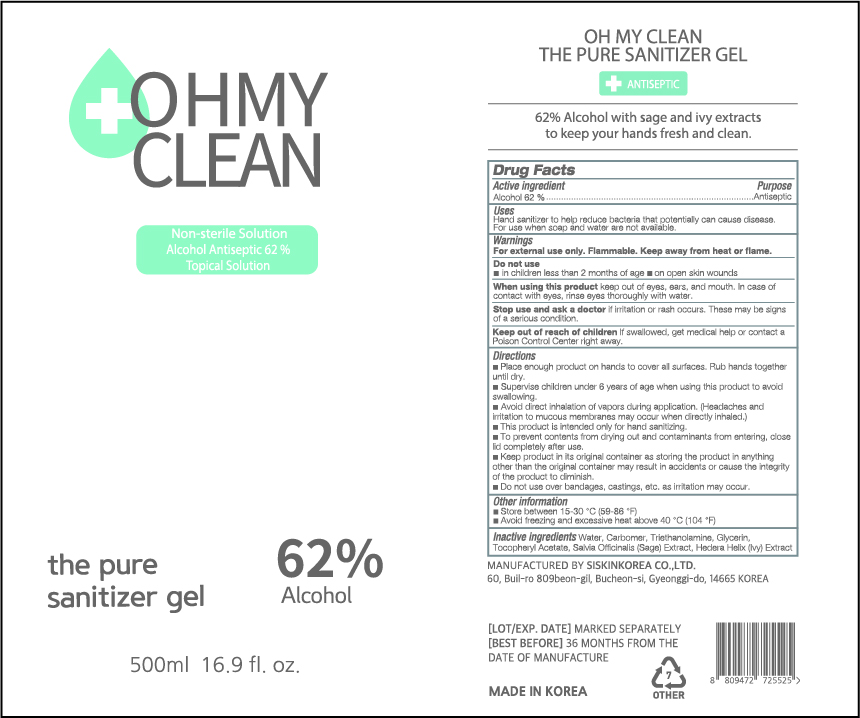 DRUG LABEL: OH MY CLEAN THE PURE SANITIZER Gel
NDC: 74514-0562 | Form: GEL
Manufacturer: SISKINKOREA CO.,LTD.
Category: otc | Type: HUMAN OTC DRUG LABEL
Date: 20200402

ACTIVE INGREDIENTS: ALCOHOL 310 mL/500 mL
INACTIVE INGREDIENTS: TROLAMINE; GLYCERIN; .ALPHA.-TOCOPHEROL ACETATE; SAGE; WATER; HEDERA HELIX LEAF; CARBOMER HOMOPOLYMER, UNSPECIFIED TYPE

500ml_62%_gel_OH MY CLEAN THE PURE SANITIZER GEL [74514-0562-1]